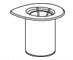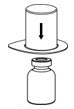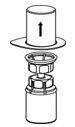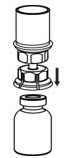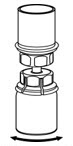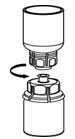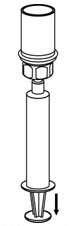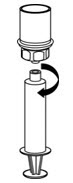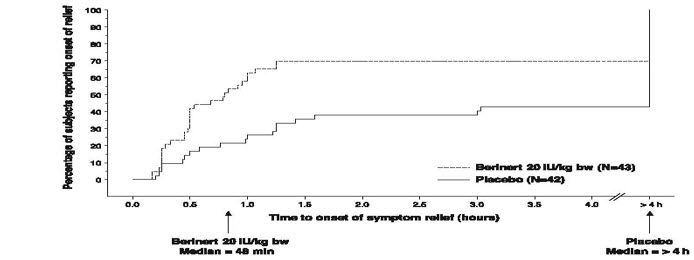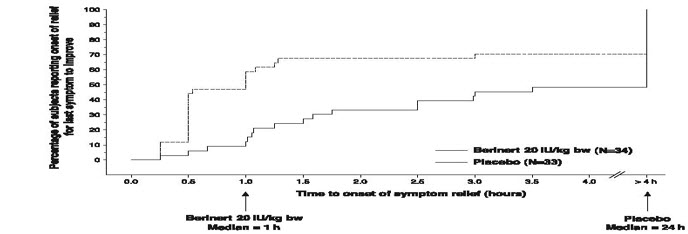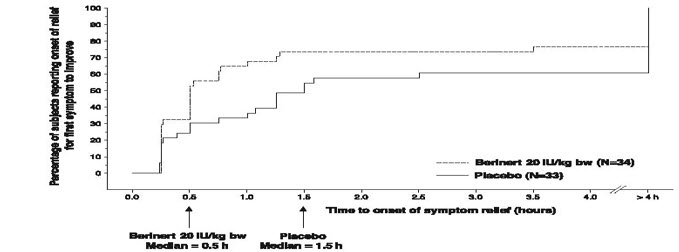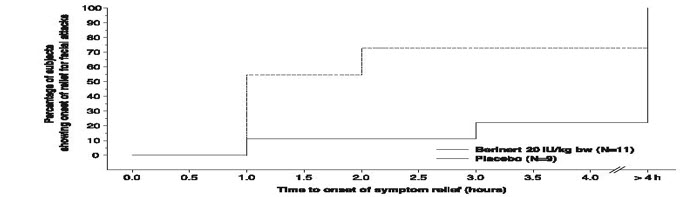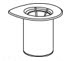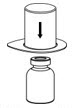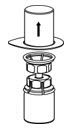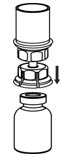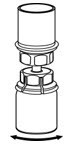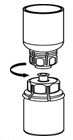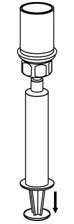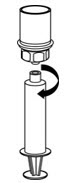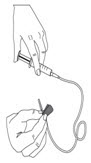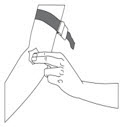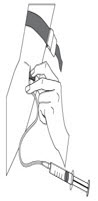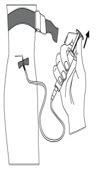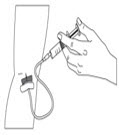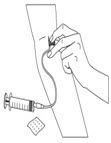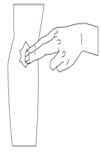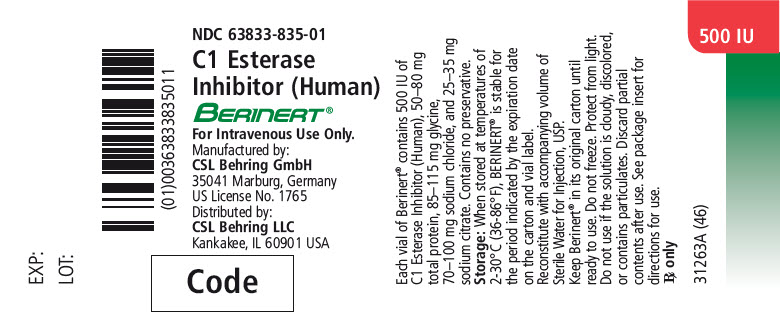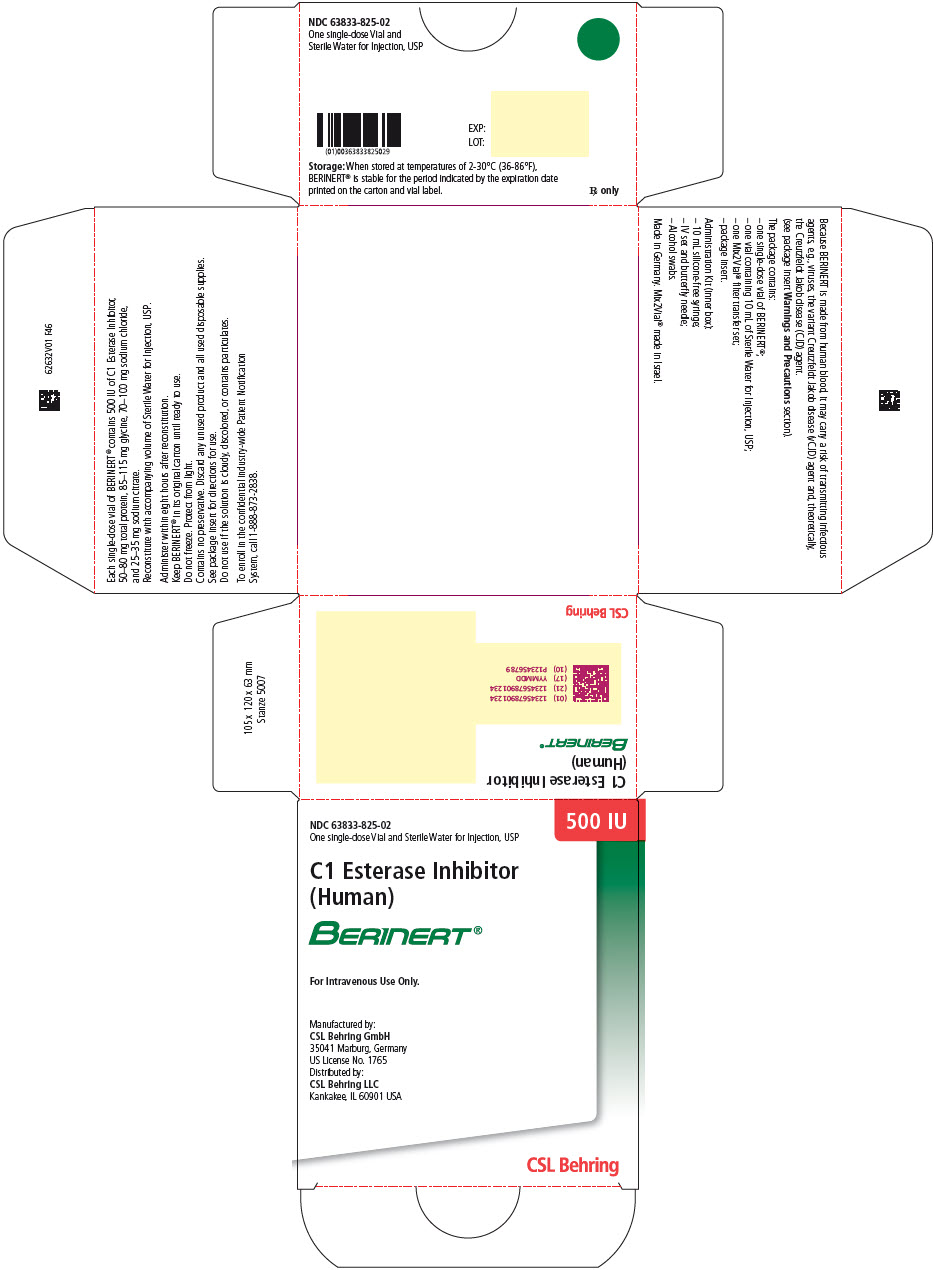 DRUG LABEL: Berinert
NDC: 63833-825 | Form: KIT | Route: INTRAVENOUS
Manufacturer: CSL Behring GmbH
Category: other | Type: PLASMA DERIVATIVE
Date: 20210921

ACTIVE INGREDIENTS: HUMAN C1-ESTERASE INHIBITOR 500 [iU]/10 mL
INACTIVE INGREDIENTS: Glycine 115 mg/10 mL; Sodium Chloride 35 mg/10 mL; SODIUM CITRATE, UNSPECIFIED FORM 100 mg/10 mL; Water

HIGHLIGHTS OF PRESCRIBING INFORMATION

These highlights do not include all the information needed to use BERINERT safely and effectively. See full prescribing information for BERINERT.
BERINERT [C1 Esterase Inhibitor (Human)]
For intravenous use. Freeze-Dried Powder for Reconstitution.
Initial U.S. Approval: 2009

RECENT MAJOR CHANGES

Dosage and Administration (2.1) | 09/2021

1 INDICATIONS AND USAGE

BERINERT is a plasma-derived C1 Esterase Inhibitor (Human) indicated for the treatment of acute abdominal, facial, or laryngeal hereditary angioedema (HAE) attacks in adult and pediatric patients. (1)

The safety and efficacy of BERINERT for prophylactic therapy have not been established. (1)

2 DOSAGE AND ADMINISTRATION

For intravenous use only.

- Store the vial in the original carton in order to protect from light. Store at 2-30°C (36-86°F). Do not freeze. (2)
- Administer 20 International Units per kg body weight. (2)
- Reconstitute BERINERT prior to use using the Sterile Water for Injection, USP provided. (2.1)
- Use the silicone-free syringe provided for administration of BERINERT. (2.1)
- Administer at room temperature within 8 hours of reconstitution. (2.1)
- Inject at a rate of approximately 4 mL per minute. (2.2)
- Do not mix BERINERT with other medicinal products or solutions. (2.2)
- Appropriately trained patients may self-administer upon recognition of an HAE attack. (2.2)

3 DOSAGE FORMS AND STRENGTHS

500 International Units lyophilized concentrate in a single-dose vial for reconstitution with 10 mL of Sterile Water for Injection, USP. (3)

4 CONTRAINDICATIONS

Do not use in patients with a history of life-threatening immediate hypersensitivity reactions, including anaphylaxis, to C1 esterase inhibitor preparations. (4)

5 WARNINGS AND PRECAUTIONS

- Hypersensitivity reactions may occur. Epinephrine should be immediately available to treat any acute severe hypersensitivity reactions following discontinuation of administration. (5.1)
- Serious arterial and venous thromboembolic (TE) events have been reported at the recommended dose of C1 Esterase Inhibitor (Human) products, including BERINERT, following administration in patients with HAE. Risk factors may include the presence of an indwelling venous catheter/access device, prior history of thrombosis, underlying atherosclerosis, use of oral contraceptives or certain androgens, morbid obesity, and immobility. Benefits of treatment of HAE attacks should be weighed against the risks of TE events in patients with underlying risk factors. Monitor patients with known risk factors for TE events during and after BERINERT administration.
  TE events have also been reported following administration of a C1 Esterase Inhibitor (Human) product when used for unapproved indications at higher than recommended doses.^1 (5.2)
- Because BERINERT is made from human blood, it may carry a risk of transmitting infectious agents, e.g., viruses, the variant Creutzfeldt-Jakob disease (vCJD) agent and, theoretically, the Creutzfeldt-Jakob disease (CJD) agent. (5.3)
- Laryngeal HAE attacks: Following self-administration of BERINERT for laryngeal HAE attacks, advise patients to immediately seek medical attention. (5.4)

6 ADVERSE REACTIONS

- The most serious adverse reaction reported in subjects who received BERINERT was an increase in the severity of pain associated with HAE. (6.1)
- The most common adverse reaction reported in greater than 4% of the subjects and greater than placebo among subjects who received BERINERT in the placebo-controlled clinical trial was dysgeusia. (6.1)

To report SUSPECTED ADVERSE REACTIONS, contact the CSL Behring Pharmacovigilance Department at 1-866-915-6958 or to the FDA at 1-800-FDA-1088 or www.fda.gov/medwatch.

8 USE IN SPECIFIC POPULATIONS

- Pregnancy: Use only if clearly needed. (8.1)
- Compared to adults, when adjusted for baseline, the half-life of BERINERT was shorter and clearance (on per kg basis) was faster in children. The clinical implication of this difference is not known. (12.3)

FULL PRESCRIBING INFORMATION

1 INDICATIONS AND USAGE

BERINERT is a plasma-derived concentrate of C1 Esterase Inhibitor (Human) indicated for the treatment of acute abdominal, facial, or laryngeal hereditary angioedema (HAE) attacks in adult and pediatric patients.

The safety and efficacy of BERINERT for prophylactic therapy have not been established.

2 DOSAGE AND ADMINISTRATION

For intravenous use only.

Administer BERINERT at a dose of 20 International Units (IU) per kg body weight by intravenous injection. Doses lower than 20 IU/kg body weight should not be administered.

BERINERT is provided as a freeze-dried powder for reconstitution with the Sterile Water for Injection, USP provided. Store the vial in the original carton in order to protect from light. Do not freeze.

2.1 Preparation and Handling

- Check the expiration date on the product vial label and on the administration kit. Do not use any component that is beyond the expiration date. Do not use if any components are damaged or opened.
- Prepare and administer using aseptic techniques [see Dosage and Administration (2.2)].
- Use the silicone-free syringe, provided, for administration of BERINERT [see How Supplied/Storage and Handling (16)].
- After reconstitution and prior to administration, inspect BERINERT visually for particulate matter and discoloration. The reconstituted solution should be colorless, clear, and free from visible particles. Do not use if the solution is cloudy, discolored, or contains particulates.
- The BERINERT vial is for single use only. BERINERT contains no preservative. Any product that has been reconstituted should be used promptly. The reconstituted solution must be used within 8 hours. Discard partially used vials.
- Do not freeze the reconstituted solution.

2.2 Reconstitution and Administration

Each BERINERT vial containing 500 IU of C1 esterase inhibitor as a lyophilized concentrate for reconstitution with 10 mL of Sterile Water for Injection, USP provided.

Use either the Mix2Vial® transfer set provided with BERINERT [see How Supplied/Storage and Handling (16.1)] or a commercially available double-ended needle and vented filter spike.

Reconstitution

The procedures below are provided as general guidelines for the reconstitution and administration of BERINERT.

1. Ensure that the BERINERT vial and diluent vial are at room temperature.
2. Place the BERINERT vial, diluent vial and Mix2Vial transfer set on a flat surface.
3. Remove the flip caps from the BERINERT and diluent vials. Wipe the vial stoppers with the alcohol swab provided. Allow to dry prior to opening the Mix2Vial transfer set package.
4. Open the Mix2Vial transfer set package by peeling away the lid (Figure 1). Leave the Mix2Vial transfer set in the clear package.
  Figure 1
5. Place the diluent vial on a flat surface and hold the vial tightly. Grip the Mix2Vial transfer set together with the clear package and push the plastic spike at the blue end of the Mix2Vial transfer set firmly through the center of the stopper of the diluent vial (Figure 2).
  Figure 2
6. Carefully remove the clear package from the Mix2Vial transfer set. Make sure that you pull up only the clear package, and not the Mix2Vial transfer set (Figure 3).
  Figure 3
7. With the BERINERT vial placed firmly on a flat surface, invert the diluent vial with the Mix2Vial transfer set attached and push the plastic spike of the transparent adapter firmly through the center of the stopper of the BERINERT vial (Figure 4). The diluent will automatically transfer into the BERINERT vial.
  Figure 4
8. With the diluent and BERINERT vial still attached to the Mix2Vial transfer set, gently swirl the BERINERT vial to ensure that the BERINERT is fully dissolved (Figure 5). Do not shake the vial.
  Figure 5
9. With one hand, grasp the BERINERT-side of the Mix2Vial transfer set and with the other hand grasp the blue diluent-side of the Mix2Vial transfer set and unscrew (counter clockwise) the set into two pieces (Figure 6).
  Figure 6
10. Carefully look at reconstituted solution in each vial of BERINERT. It should be colorless, clear, and free from visible particles. Do not use the vial if the liquid looks cloudy, contains particles, or has changed color. Do not use if the expiration date on the label has expired.
11. Draw air into the empty, sterile, silicone-free syringe provided. While the BERINERT vial is upright, screw the syringe to the Mix2Vial transfer set. Inject air into the BERINERT vial. While keeping the syringe plunger pressed, invert the system upside down and draw the concentrate into the syringe by pulling the plunger back slowly (Figure 7). If BERINERT is not immediately used, please store reconstituted solution in the vial.
  Figure 7
12. Now that the concentrate has been transferred into the syringe, firmly grasp the barrel of the syringe (keeping the plunger facing down) and unscrew (counter clockwise) the syringe from the Mix2Vial transfer set (Figure 8). Attach the syringe to a suitable intravenous administration set.
  Figure 8
13. If patient requires more than one vial, a new unused Mix2Vial transfer set and a new silicone-free syringe should be used for each BERINERT vial.
14. Do not refrigerate after reconstitution. When reconstitution is carried out using aseptic technique, administration may begin within 8 hours, provided the solution has been stored at up to 30°C (86°F). Do not refrigerate or freeze the reconstituted solution. Only store the reconstituted solution in the vial.

Administration

- Do not mix BERINERT with other medicinal products. Administer BERINERT by a separate infusion line.
- Use aseptic technique when administering BERINERT.
- Use the silicone-free syringe provided in the administration kit [see How Supplied/Storage and Handling (16)].
- Follow recommended venipuncture guidelines for initiating intravenous therapy.
- Administer BERINERT by slow intravenous injection at a rate of approximately 4 mL per minute. Please refer to the illustration in step 6 of the self-administration section in the Patient Product Information (PPI) section.
- For self-administration, provide the patient with instructions and training for intravenous injection outside of a clinic setting so patients may self-administer BERINERT upon recognition of symptoms of an HAE attack [see Patient Counseling Information (17)].
- After administration, immediately discard any unused product and all used disposable supplies in accordance with local requirements.

3 DOSAGE FORMS AND STRENGTHS

- BERINERT is available in a single-dose vial that contains 500 IU of C1 esterase inhibitor as a lyophilized concentrate.
- Each vial must be reconstituted with 10 mL of Sterile Water for Injection, USP provided.

4 CONTRAINDICATIONS

BERINERT is contraindicated in individuals who have experienced life-threatening hypersensitivity reactions, including anaphylaxis, to C1 esterase inhibitor preparations.

5 WARNINGS AND PRECAUTIONS

5.1 Hypersensitivity

Severe hypersensitivity reactions may occur. Epinephrine should be immediately available for treatment of acute severe hypersensitivity reaction [see Patient Counseling Information (17)]. The signs and symptoms of hypersensitivity reactions may include hives, generalized urticaria, tightness of the chest, wheezing, hypotension, and/or anaphylaxis during or after injection of BERINERT.

Because hypersensitivity reactions may have symptoms similar to HAE attacks, treatment methods should be carefully considered. In case of suspected hypersensitivity, immediately discontinue administration of BERINERT and institute appropriate treatment.

5.2 Thromboembolic Events

Serious arterial and venous thromboembolic (TE) events have been reported at the recommended dose of C1 Esterase Inhibitor (Human) products, including BERINERT, following administration in patients with HAE. Risk factors may include the presence of an indwelling venous catheter/access device, prior history of thrombosis, underlying atherosclerosis, use of oral contraceptives or certain androgens, morbid obesity, and immobility. Benefits of treatment of HAE attacks should be weighed against the risks of TE events in patients with underlying risk factors. Monitor patients with known risk factors for TE events during and after BERINERT administration.

TE events have also been reported following administration of a C1 Esterase Inhibitor (Human) product when used for unapproved indications at higher than recommended doses^1,2 [see Overdosage (10) and Nonclinical Toxicology (13.2)].

5.3 Transmissible Infectious Agents

Because BERINERT is made from human blood, it may carry a risk of transmitting infectious agents, e.g., viruses, the variant Creutzfeldt-Jakob disease (vCJD) agent and, theoretically, the Creutzfeldt-Jakob disease (CJD) agent. The risk that such products will transmit an infectious agent has been minimized by screening plasma donors for prior exposure to certain viruses, by testing for the presence of certain current virus infections, and by processes demonstrated to inactivate and/or remove a wide range of viruses [see Description (11)].

Despite these measures, such products may still potentially transmit disease and there is also the possibility that unknown infectious agents may be present in such products. However, since implementation of these measures, no case reports on suspected transmission of viruses have demonstrated a causal relationship to the administration of BERINERT.

All infections thought by a physician possibly to have been transmitted by BERINERT should be reported by lot number, by the physician, or other healthcare provider to the CSL Behring Pharmacovigilance Department at 1-866-915-6958.

5.4 Laryngeal HAE Attacks

Given the potential for airway obstruction during acute laryngeal HAE attacks, patients self-administering BERINERT should be advised to immediately seek medical attention in an appropriate healthcare facility after treatment with BERINERT.

6 ADVERSE REACTIONS

The most serious adverse reaction reported in subjects enrolled in clinical studies who received BERINERT was an increase in the severity of pain associated with HAE.

The most common adverse reaction reported in greater than 4% of the subjects and greater than placebo among subjects who received BERINERT in the placebo-controlled clinical trial was dysgeusia.

6.1 Clinical Trials Experience

Because clinical studies are conducted under widely varying conditions, adverse reaction rates observed in the clinical trials of a drug cannot be directly compared to rates in the clinical trials of another drug and may not reflect the rates observed in practice.

Placebo-controlled Clinical Study

In the placebo-controlled clinical study, referred to as the randomized clinical trial (RCT) [see Clinical Studies (14)], 124 subjects experiencing an acute moderate to severe abdominal or facial HAE attack were treated with BERINERT (either a 10 IU per kg body weight or a 20 IU per kg body weight dose), or placebo (physiological saline solution).

The treatment-emergent serious adverse reactions/events that occurred in 5 subjects in the RCT were laryngeal edema, facial HAE attacks with laryngeal edema, swelling (shoulder and chest), exacerbation of hereditary angioedema, and laryngospasm.

After initial infusion or rescue Medication treatment with BERINERT versus placebo, in the intent-to-treat population only one adverse reaction was reported in greater than one subject in either treatment group, at a frequency higher than placebo: dysgeusia was reported within 4 hours of infusion of BERINERT versus placebo (2/43, 4.7% vs. 0/42, 0%) and up to 72 hours (2/43, 4.7% vs. 1/42, 2.4%). Because more subjects in the placebo group than in the BERINERT group received rescue treatment, the median observation period in this analysis for subjects randomized to placebo was slightly longer than for subjects randomized to receive BERINERT.

Subjects were tested at baseline and after 3 months for possible exposure to Parvovirus B19, hepatitis B, hepatitis C, and HIV-1 and HIV-2. No subject who underwent testing evidenced seroconversion or treatment-emergent positive polymerase chain reaction testing for these pathogens.

Open-Label Extension Study

In the safety analysis of the open-label extension study, 57 subjects with 1085 acute moderate to severe abdominal, facial, peripheral, and laryngeal HAE attacks received a 20 IU/kg body weight dose of BERINERT [see Clinical Studies (14)]. This study provides additional safety data in subjects who received multiple infusions of the product for sequential HAE attacks (one infusion per attack).

Table 1 lists the adverse reactions that occurred in the safety analysis of the open-label extension study in ≥2 subjects or associated with ≥5 HAE attacks during infusion or within 24 hours or 72 hours after the end of a BERINERT infusion.

Table 1. Incidence of subjects and HAE Attacks with Adverse Reactions (ARs) [Because of the allowance of rescue medication in both study arms, all listed adverse events were considered to be at least potentially related to study medication (e.g., adverse reactions), regardless of the investigator's opinion concerning causality.] Starting during Infusion or Within 24 hours or 72 hours after End of an Infusion (Experienced by ≥2 subjects or Associated with ≥5 HAE Attacks Overall) by Preferred Term (Safety subject and HAE Attack Populations) – Open-Label Extension Study
 | Number (%) of subjects (n=57) |  | Number (%) of Attacks (n=1085)
Preferred term | ARs within 24 hours | ARs within 72 hours | ARs within 24 hours | ARs within 72 hours
Any preferred term | 13 (22.8%) | 20 (35.1%) | 27 (2.5%) | 41 (3.8%)
Headache | 2 (3.5%) | 4 (7.0%) | 3 (0.3%) | 6 (0.6%)
Nasopharyngitis | 1 (1.8%) | 2 (3.5%) | 1 (<0.1%) | 2 (0.2%)
Abdominal pain or discomfort | 1 (1.8%) | 3 (5.3%) | 2 (0.2%) | 6 (0.6%)
Upper respiratory tract infection | 0 (0) | 1 (1.8%) | 0 (0) | 1 (<0.1%)
Hereditary angioedema attack [Hereditary angioedema attacks were only to be reported as adverse reaction if it was a worsening of symptoms during a treated HAE attack. New HAE attacks were not to be reported as adverse reactions. Although the adverse reaction of hereditary angioedema in subject 22301 was a new HAE attack that started after the previous HAE attack had completely resolved, this HAE attack was reported as an adverse reaction, because the HAE attack was not included in the study and treated outside study site with medication other than the study medication.] | 1 (1.8%) | 1 (1.8%) | 1 (<0.1%) | 1 (<0.1%)
Influenza like illness | 1 (1.8%) | 2 (3.5%) | 1 (<0.1%) | 2 (0.2%)
Rash | 2 (3.5%) | 2 (3.5%) | 2 (0.2%) | 2 (0.2%)
Vulvovaginal mycotic infection | 0 (0) | 2 (3.5%) | 0 (0) | 2 (0.2%)
Nausea | 1 (1.8%) | 1 (1.8%) | 4 (0.4%) | 5 (0.5%)
N = total number of subjects/HAE attacks
Data are sorted by decreasing frequency by number of subjects.

The incidence and type of adverse reactions with BERINERT when administered for treatment of multiple consecutive acute HAE attacks of any type was similar to those previously observed. As in the placebo-controlled study, no proven cases of infections due to HIV-1/2, HAV, HBV, HCV or Parvovirus B19 were observed during the study.

6.2 Immunogenicity

In a post-marketing study forty-six subjects with Type I or Type II HAE were monitored for inhibitory or non-inhibitory antibodies to C1-INH. Blood samples for antibody assessment were taken at Day 1 (First HAE attack requiring administration of a dose of 20 IU/kg IV, baseline value), and at 3, 6 and 9 months. No subjects developed inhibitory antibodies to C1-INH at any of the time points following infusion of BERINERT. Thirteen subjects (28.2%), however, had detectable levels of non-inhibitory Abs at some point during the study, including 9 subjects (19.6%) who had detectable non-inhibitory Abs at baseline. The presence of non-inhibitory anti-C1-INH Abs did not induce apparent immunologically-associated clinical events.

The detection of antibody formation is highly dependent on the sensitivity and specificity of the assay. Additionally, the observed incidence of antibody (including neutralizing antibody) positivity in an assay may be influenced by several factors including assay methodology, sample handling, timing of sample collection, concomitant medications, and underlying disease. For these reasons, it may be misleading to compare the incidence of antibodies to BERINERT in the studies described above with the incidence of antibodies in other studies or to other products.

6.3 Postmarketing Experience

Because postmarketing reporting of adverse reactions is voluntary and from a population of uncertain size, it is not always possible to reliably estimate the frequency of these reactions or establish a causal relationship to product exposure.

Adverse reactions reported in Europe since 1979 in patients receiving BERINERT for treatment of HAE include hypersensitivity/anaphylactic reactions, injection-site pain, injection-site redness, chills, and fever.

TE Events Associated with HAE Treatment

TE events including basilar artery thrombosis, multiple pulmonary microemboli, and thrombosis have been reported with the use of BERINERT at the recommended dose following treatment of HAE.

TE Events Associated with Use in Unapproved Indications

TE events have also been reported with the use of BERINERT in patients receiving higher than recommended doses during cardiac surgery (unapproved indication) include carotid artery thrombosis, cerebral thrombosis, myocardial infarction, pulmonary embolism, renal vein thrombosis, sagittal sinus thrombosis, inferior vena cava thrombosis, superior vena cava thrombosis, internal jugular vein thrombosis, and peripheral venous thrombosis.^1

The following adverse reactions, identified by system organ class, have been attributed to BERINERT during post-approval use outside the US.

- Immune System Disorder: Hypersensitivity/anaphylactic reactions, and shock
- General/Body as a Whole: Pain on injection, redness at injection site, chills, and fever

8 USE IN SPECIFIC POPULATIONS

8.1 Pregnancy

Risk Summary

Background risk (general population)

A review of available data suggests that major birth defects occur in 2-4% of the U.S. general population and that miscarriage occurs in 15-20% of clinically recognized pregnancies, regardless of drug exposure.

Data

Risk in BERINERT patients

In a retrospective case collection study, 20 pregnant women ranging in age from 20 to 35 years received BERINERT with repeated doses up to 3,500 IU per HAE attack; these women reported no complications during delivery and no harmful effects on their 34 neonates.^3 BERINERT should be given to a pregnant woman only if clearly needed.

8.2 Lactation

Risk Summary

It is not known whether BERINERT is excreted in human milk. Because many drugs are excreted in human milk, caution should be exercised when BERINERT is administered to a nursing woman.

8.4 Pediatric Use

Safety and efficacy of BERINERT have been evaluated in 12 pediatric patients with HAE (age range 10 to 16 years) in the placebo controlled and open-label extension studies. BERINERT was also evaluated in 18 pediatric patients with HAE (age range 5 to 11 years) in a Registry Study conducted in the US and Europe. The safety profile observed in the pediatric population was similar to that observed in adults. The pharmacokinetics of BERINERT were evaluated in 5 pediatric subjects (ages 6 through 13) [see Clinical Pharmacology (12.3)].

8.5 Geriatric Use

The safety and efficacy of BERINERT in the geriatric population have not been evaluated in controlled clinical studies. BERINERT was evaluated in 27 geriatric subjects (age range 65 to 83 years) with HAE in a Registry Study conducted in the US and Europe. The safety profile observed in the geriatric population was similar to that observed in the younger populations studied.

10 OVERDOSAGE

The development of thrombosis has been reported after doses exceeding 20 IU/kg body weight of BERINERT when used for unapproved indications in newborns and young children with congenital heart anomalies during or after cardiac surgery under extracorporeal circulation.^1

The maximum dose administered in clinical studies in hereditary angioedema was 20 IU/kg body weight.

11 DESCRIPTION

BERINERT is a human plasma-derived, purified, pasteurized, lyophilized concentrate of C1 esterase inhibitor to be reconstituted for intravenous administration. BERINERT is prepared from large pools of human plasma from US donors. The potency of C1 esterase inhibitor is expressed in International Units (IU), which is related to the current WHO Standard for C1 esterase inhibitor products.

C1 esterase inhibitor is a soluble, single-chain glycoprotein containing 478 amino acid residues organized into three beta-sheets and eight or nine alpha-helices.^4 The heavily glycosylated molecule has an apparent molecular weight of 105 kD, of which the carbohydrate chains comprise 26% to 35%.^5

Each 500 IU vial of reconstituted BERINERT contains 400-625 IU C1 esterase inhibitor, 50 to 80 mg total protein, 85 to 115 mg glycine, 70 to 100 mg sodium chloride, and 25 to 35 mg sodium citrate.

All plasma used in the manufacture of BERINERT is obtained from US donors and is tested using serological assays for hepatitis B surface antigen and antibodies to HIV-1/2 and HCV. Additionally, the plasma is tested with Nucleic Acid Testing (NAT) for HBV, HCV, HIV-1 and HAV and found to be non-reactive (negative). In addition, the plasma is also tested by NAT for Human Parvovirus B19. Only plasma that has passed virus screening is used for production, and the limit for Parvovirus B19 in the fractionation pool is set not to exceed 10^4 IU of Parvovirus B19 DNA per mL.

The manufacturing process for BERINERT includes multiple steps that reduce the risk of virus transmission. The virus inactivation/reduction capacity consists of three steps:

- Pasteurization in aqueous solution at 60°C for 10 hours
- Hydrophobic interaction chromatography
- Virus filtration (also called nanofiltration) by two filters, 20 nm and 15 nm, in series

This was evaluated in a series of in vitro spiking experiments. The total mean cumulative virus inactivation/reduction is shown in Table 2.

Table 2. Mean Virus Inactivation/Reductions in BERINERT
Virus Studied | Pasteurization [log10] | Hydrophobic Interaction Chromatography [log10] | Virus Filtration [log10] | Total Cumulative [log10]
Enveloped Viruses
HIV-1 | ≥6.6 | ≥4.5 | ≥5.1 | ≥16.2
BVDV | ≥9.2 | ≥4.7 | ≥5.3 | ≥19.2
PRV | 6.3 | ≥6.5 | ≥7.1 | ≥19.9
WNV | ≥7.0 | ND | ≥8.0 | ≥15.0
Non-Enveloped Viruses
HAV | ≥6.4 | 2.8 | ≥5.3 | ≥14.5
CPV | 1.4 | 3.9 | 7.1 | 12.4
B19V | 3.9 | ND | ND | NA
HIV-1, Human immunodeficiency virus type 1, a model for HIV-1 and HIV-2
BVDV, Bovine viral diarrhea virus, a model for HCV
PRV, Pseudorabies virus, a model for large enveloped DNA viruses
WNV, West Nile virus
HAV, Hepatitis A virus
CPV, Canine parvovirus
B19V, Human Parvovirus B19
ND, Not determined
NA, Not applicable

12 CLINICAL PHARMACOLOGY

12.1 Mechanism of Action

C1 esterase inhibitor is a normal constituent of human plasma and belongs to the group of serine protease inhibitors (serpins) that includes antithrombin III, alpha1-protease inhibitor, alpha2-antiplasmin, and heparin cofactor II. As with the other inhibitors in this group, C1 esterase inhibitor has an important inhibiting potential on several of the major cascade systems of the human body, including the complement system, the intrinsic coagulation (contact) system, the fibrinolytic system, and the coagulation cascade. Regulation of these systems is performed through the formation of complexes between the proteinase and the inhibitor, resulting in inactivation of both and consumption of the C1 esterase inhibitor.

C1 esterase inhibitor, which is usually activated during the inflammatory process, inactivates its substrate by covalently binding to the reactive site. C1 esterase inhibitor is the only known inhibitor for the subcomponent of the complement component 1 (C1r), C1s, coagulation factor XIIa, and kallikrein. Additionally, C1 esterase inhibitor is the main inhibitor for coagulation factor XIa of the intrinsic coagulation cascade.

HAE patients have low levels of endogenous or functional C1 esterase inhibitor. Although the events that induce HAE attacks of angioedema in HAE patients are not well defined, it has been postulated that increased vascular permeability and the clinical manifestation of HAE attacks may be primarily mediated through contact system activation. Suppression of contact system activation by C1 esterase inhibitor through the inactivation of plasma kallikrein and factor XIIa is thought to modulate this vascular permeability by preventing the generation of bradykinin.^6

Administration of BERINERT to patients with C1 esterase inhibitor deficiency replaces the missing or malfunctioning protein in patients. The plasma concentration of C1 esterase inhibitor in healthy volunteers is approximately 270 mg/L.^7

12.3 Pharmacokinetics

The pharmacokinetics of BERINERT were evaluated in an open-label, uncontrolled, single-center study in 40 subjects (35 adults and 5 children under 16 years of age) with either mild or severe HAE. All subjects received a single intravenous injection of BERINERT ranging from 500 IU to 1500 IU. Blood samples were taken during an HAE attack-free period at baseline and for up to 72 hours after drug administration. Pharmacokinetic parameters were estimated using non-compartmental analysis (with or without baseline adjustment). Table 3 summarizes the pharmacokinetic parameters in 35 adult subjects with HAE.

Table 3. Pharmacokinetic Parameters of BERINERT in Adult subjects with HAE by Non-compartmental Analysis (n=35)
Parameters | Unadjusted for baseline | Adjusted for baseline
AUC(0-t) (hr × IU/mL) [Based on a 15 IU/kg dose. Numbers in parenthesis are the range.] | 27.5 ± 8.5 (15.7-44.7) | 12.8 ± 6.7 (3.9-34.7)
CL (mL/hr/kg) | 0.60 ± 0.17 (0.34-0.96) | 1.44 ± 0.67 (0.43-3.85)
Vss (mL/kg) | 18.6 ± 4.9 (11.1-27.6) | 35.4 ± 10.5 (14.1-56.1)
Half-life (hrs) | 21.9 ± 1.7 (16.5-24.4) | 18.4 ± 3.5 (7.4-22.8)
MRT (hrs) | 31.5 ± 2.4 (23.7-35.2) | 26.4 ± 5.0 (10.7-33.0)
AUC: Area under the curve
CL: Clearance
Vss: Volume steady state
MRT: Mean residence time

Table 4 summarizes the pharmacokinetic parameters in 5 pediatric subjects (ages 6 through 13) with HAE. When adjusted for baseline, compared to adults, the half-life of BERINERT was shorter and clearance (on per kg basis) was faster in this limited cohort of children. However, the clinical implication of this difference is not known.

Table 4. Pharmacokinetic Parameters of BERINERT in Pediatric subjects (n=5) [Age Range: 6-13 years] with HAE by Non-compartmental Analysis
Parameters | Unadjusted for baseline | Adjusted for baseline
AUC(0-t) (hr × IU/mL) [Based on a 15 IU/kg dose. Numbers in parenthesis are the range.] | 25.45 ± 5.8 (16.8-31.7) | 9.78 ± 4.37 (4.1-15.2)
CL (mL/hr/kg) | 0.62 ± 0.17 (0.47-0.89) | 1.9 ± 1.1 (0.98-3.69)
Vss (mL/kg) | 19.8 ± 4.0 (16.7-26.1) | 38.8 ± 8.9 (31.9-54.0)
Half-life (hrs) | 22.4 ± 1.6 (20.3-24.4) | 16.7 ± 5.8 (7.4-22.5)
MRT (hrs) | 32.3 ± 2.3 (29.3-35.2) | 24.0 ± 8.3 (10.7-32.4)
AUC: Area under the curve
CL: Clearance
Vss: Volume steady state
MRT: Mean residence time

Studies have not been conducted to evaluate the pharmacokinetics of BERINERT in special patient populations identified by gender, race, geriatric age, or the presence of renal or hepatic impairment.

13 NONCLINICAL TOXICOLOGY

13.1 Carcinogenesis, Mutagenesis, Impairment of Fertility

No animal studies have been completed to evaluate the effects of BERINERT on carcinogenesis, mutagenesis, and impairment of fertility.

13.2 Animal Toxicology and/or Pharmacology

Acute intravenous toxicity of BERINERT was performed in mice at 1500, 3000, and 6000 IU/kg and in rats at 1000, 2000, and 3000 IU/kg. BERINERT was well tolerated and no signs of toxicity were observed up to the highest dose administered.

Repeat intravenous dose toxicity was studied in a 14-day repeat dose study in rats at doses of 20, 60, and 200 IU/kg/day. BERINERT was well tolerated and no toxicity was observed up to the highest dose administered. No antibody response against C1 esterase inhibitor could be demonstrated in this study after multiple dosing with BERINERT.

In a safety pharmacology study, BERINERT was administered to beagle dogs intravenously at a cumulative dose of 3500 IU/kg. No adverse effects were seen on the cardiovascular and respiratory system. There was a drop in body temperature, reduced coagulation time, and a decrease in thrombocyte aggregation.

Local intravenous tolerance of BERINERT was evaluated in rabbits at 1500 IU. No pathological changes were noted at the time of injection or during the following 24 hours. No pathological signs were noted during necropsy.

A study in pigs investigating cardioprotective effects of C1 esterase inhibitor suggests a risk of thrombosis from intravenous administration of C1 esterase inhibitor products at doses of 200 IU/kg; however, in this model, cardioprotective effects were observed at a dose of 40 IU/kg.^2

14 CLINICAL STUDIES

The safety and efficacy of BERINERT in the treatment of acute abdominal or facial HAE attacks in subjects with hereditary angioedema were demonstrated in a placebo-controlled, double-blind, prospective, multinational, randomized, parallel-group, dose-finding, three-arm, clinical study, referred to as the randomized clinical trial (RCT). The RCT assessed the efficacy and safety of BERINERT in 124 adult and pediatric subjects with C1 esterase inhibitor deficiency who were experiencing an acute moderate to severe attack of abdominal or facial HAE. Subjects ranged in age from six to 72 years of age; 67.7% were female and 32.3% were male; and approximately 90% were Caucasian.

The study objectives were to evaluate whether BERINERT shortens the time to onset of relief of symptoms of an abdominal or facial HAE attack compared to placebo and to compare the efficacy of two different doses of BERINERT. The time to onset of relief of symptoms was determined by the subject's response to a standard question posed at appropriate time intervals for as long as 24 hours after start of treatment, taking into account all single HAE symptoms. In addition, the severity of individual HAE symptoms was assessed over time.

Subjects were randomized to receive a single 10 IU/kg body weight dose of BERINERT (39 subjects), a single 20 IU/kg dose of BERINERT (43 subjects), or a single dose of placebo (42 subjects) by slow intravenous infusion (recommended to be given at a rate of approximately 4 mL per minute) within 5 hours of an HAE attack. At least 70% of the subjects in each treatment group were required to be experiencing an abdominal HAE attack.

If a subject experienced no relief or insufficient relief of symptoms by 4 hours after infusion, investigators had the option to administer a second infusion of BERINERT (20 IU/kg for the placebo group, 10 IU/kg for the 10 IU/kg group), or placebo (for the 20 IU/kg group). This masked (blinded) "rescue study medication" was administered to subjects and they were then followed until complete resolution of symptoms was achieved. Adverse events were collected for up to 7 to 9 days following the initial administration of BERINERT or placebo.

In the rare case that a subject developed life-threatening laryngeal edema after inclusion into the study, immediate start of open-label treatment with a 20 IU/kg body weight dose of BERINERT was allowed.

All subjects who received confounding medication (rescue medication) before symptom relief were regarded as "non-responders". Therefore, time to onset of symptom relief was set at 24 hours if a subject received any rescue medication (ie, rescue study medication, narcotic analgesics, non-narcotic analgesics, anti-emetics, open-label C1 inhibitor, androgens at increased dose, or fresh frozen plasma) between 5 hours before administration of blinded study medication until time to onset of relief.

For the trial to be considered successful, the study protocol specified the following criteria for the differences between the BERINERT 20 IU/kg and the placebo group:

- The time to onset of relief of symptoms of the HAE attack had to achieve a one-sided p-value of less than 0.0249 for the final analysis, and at least one of the following criteria had to demonstrate a trend in favor of BERINERT with a one-sided p-value of less than 0.1:
  - The proportion of subjects with increased intensity of clinical HAE symptoms between 2 and 4 hours after start of treatment with study medication compared to baseline, or
  - The number of vomiting episodes within 4 hours after start of study treatment.

Subjects treated with 20 IU/kg body weight of BERINERT experienced a significant reduction (p=0.0016; "Wilcoxon Rank Sum test") in time to onset of relief from symptoms of an HAE attack as compared to placebo (median of 48 minutes for BERINERT 20 IU/kg body weight, as compared to a median of >4 hours for placebo). The time to onset of relief from symptoms of an HAE attack for subjects in the 10 IU/kg dose of BERINERT was not statistically significantly different from that of subjects in the placebo group.

Figure 9 is a Kaplan-Meier curve showing the percentage of subjects reporting onset of relief of HAE attack symptoms as a function of time. Individual time points beyond 4 hours are not presented on the graph because the protocol permitted blinded rescue medication, analgesics, and/or anti-emetics to be administered starting 4 hours after randomized blinded study medication had been administered.

Figure 9. Time to Onset of Symptom Relief with Imputation to >4 hours for subjects Who Received any Rescue Medication [Included rescue study medication (as blinded C1 inhibitor or placebo given as rescue medication), open-label C1 inhibitor, narcotic and non-narcotic analgesics, anti-emetics, androgens at increased dose, or fresh frozen plasma.] or Non-narcotic Analgesics Before Start of Relief

In addition, the efficacy of BERINERT 20 IU/kg body weight could be confirmed by observing a reduction in the intensity of single HAE symptoms at an earlier time compared to placebo. For abdominal attacks Figure 10 shows the time to start of relief of the last symptom to improve that was already present at baseline. Pre-defined abdominal HAE symptoms included pain, nausea, vomiting, cramps and diarrhea. Figure 11 shows the respective time to start of relief of the first symptom to improve that was already present at baseline.

Figure 10. Time to Start of Relief of the Last Symptom to Improve (Abdominal HAE Attacks) with Imputation to >4 hours for subjects Who Received any Rescue Medication [Included rescue study medication (as blinded C1 inhibitor or placebo given as rescue medication), open-label C1 inhibitor, narcotic and non-narcotic analgesics, anti-emetics, androgens at increased dose, or fresh frozen plasma.] Before Start of Relief

Figure 11. Time to Start of Relief of the First Symptom to Improve (Abdominal HAE Attacks) with Imputation to >4 hours for subjects Who Received Any Rescue Medication [Included rescue study medication (as blinded C1 inhibitor or placebo given as rescue medication), open-label C1 inhibitor, narcotic and non-narcotic analgesics, anti-emetics, androgens at increased dose, or fresh frozen plasma.] Before Start of Relief

For facial attacks, single HAE symptoms were recorded. In addition, photos were taken at pre-determined time points and assessed by the members of an independent Data Safety Monitoring Board (DSMB), who were blinded as to treatment, center and other outcome measures. The change in the severity of the edema when compared to baseline was assessed on a scale with outcomes "no change", "better", "worse" and "resolved". Figure 12 shows the time to start of relief from serial facial photographs by DSMB assessment.

Figure 12. Time to Start of Relief from Serial Facial Photographs [Includes facial HAE attacks in subjects with concomitant abdominal HAE attacks.]

Table 5 compares additional endpoints, including changes in HAE symptoms and use of rescue medication in subjects receiving BERINERT at 20 IU/kg body weight and placebo.

Table 5. Changes in HAE Symptoms and Use of Rescue Medication in subjects Receiving BERINERT 20 IU/kg Body Weight vs. Placebo
Additional Endpoints | Number (%) of subjects BERINERT 20 IU/kg Body Weight Group (n=43) | Number (%) of subjects Placebo Group (n=42)
Onset of symptom relief within 60 minutes after administration of study medication (post-hoc) | 27 (62.8%) | 11 (26.2%)
Onset of symptom relief within 4 hours after administration of study medication | 30 (69.8%) | 18 (42.9%)
Number of vomiting episodes within 4 hours after start of study treatment [p-value = 0.033] | 6 episodes | 35 episodes
Worsened intensity of clinical HAE symptoms between 2 and 4 hours after administration of study medication compared to baseline [p-value = 0.00008] | 0 (0%) | 12 (28.6%)
Number (percent) of combined abdominal and facial HAE attack subjects receiving rescue study medication, analgesics, or anti-emetics at any time prior to initial relief of symptoms | 13 (30.2%) | 23 (54.8%)
At least one new HAE symptom not present at baseline and starting within 4 hours after administration of study medication | 2 (4.6%) | 6 (14.3%)

Both the proportion of subjects with increased intensity of clinical HAE symptoms between 2 and 4 hours after start of treatment compared to baseline, and the number of vomiting episodes within 4 hours after start of study treatment demonstrated trends in favor of BERINERT in comparison to placebo (p-values <0.1). Tables 6 through 9 present additional information regarding responses to treatment.

Table 6. Proportion of subjects Experiencing Start of Self-Reported Relief of Symptoms by 4 hours by HAE Attack Type
HAE Attack Type | BERINERT 20 IU/kg Body Weight (Abdominal subjects = 34) (Facial subjects = 9) (Other subjects = 0) | Placebo Group (Abdominal subjects = 33) (Facial subjects = 8) (Other subjects = 1) [Laryngeal edema initially classified as facial edema.]
Abdominal | 24 (70.6%) | 15 (45.5%)
Facial | 6 (66.7%) | 3 (37.5%)

Table 7. Proportion of subjects Experiencing Reduction in Severity of at Least One Individual HAE Attack Symptom by 4 hours
HAE Attack Type | BERINERT 20 IU/kg Body Weight (Abdominal subjects = 34) (Facial subjects = 9) | Placebo Group (Abdominal subjects = 33) (Facial subjects = 8)
Abdominal | 33 (97.1%) | 29 (87.9%)
Facial | 6 (66.7%) | 4 (50%)

Table 8. Proportion of subjects with Facial HAE Attacks Demonstrating Improvement in Serial Facial Photographs by 4 hours [Based on masked (blinded) evaluation by data safety monitoring board.]
Attack Type | BERINERT 20 IU/kg Body Weight (Subjects = 9) | Placebo Group (Subjects = 8)
Facial | 7 (77.8%) | 2 (25%)

Table 9. Proportion of subjects with Abdominal and Facial HAE Attacks Receiving Rescue Study Medication at any Time Prior to Complete Relief of Symptoms
HAE Attack Type | BERINERT 20 IU/kg Body Weight | Placebo Group
HAE Attack Type | (Abdominal subjects = 34) (Facial subjects = 9) | (Abdominal subjects = 33) (Facial subjects = 8)
Abdominal | 7 (20.6%) | 17 (51.5%)
Facial | 1 (11.1%) | 6 (75%)

No subjects treated with BERINERT at 20 IU/kg body weight reported worsening of symptoms at 4 hours after administration of study medication compared to baseline.

The study demonstrated that the BERINERT 20 IU/kg body weight dose was significantly more efficacious than the BERINERT 10 IU/kg body weight dose or placebo.

Open-Label Extension Study

BERINERT was evaluated in a prospective, open-label, uncontrolled, multicenter extension study conducted at 15 centers in the US and Canada in subjects who had participated in the RCT study for the treatment of acute abdominal or facial HAE attacks in subjects with hereditary angioedema.

The purpose of this extension study was to provide BERINERT to subjects who had participated in the RCT study and who experienced any type of subsequent HAE attack (ie, abdominal, facial, peripheral, or laryngeal).

The safety analysis of the open-label extension study included a total of 57 subjects (19 males and 38 females, age range: 10 to 53 years) with 1085 HAE attacks treated with 20 IU/kg body weight dose of BERINERT per attack, who were observed at the study site until onset of relief of HAE symptoms, and were followed up for adverse reactions for 7 to 9 days following treatment of each HAE attack [see Adverse Reactions (6.1)]. During the extension study, 51 subjects experienced 747 abdominal attacks, 21 subjects experienced 51 facial HAE attacks, 30 subjects experienced 235 peripheral HAE attacks, and 16 subjects experienced 48 laryngeal HAE attacks. Some study subjects may have experienced HAE attacks in more than one location.

An analysis of laryngeal HAE attacks showed that the median time to initial onset of symptom relief and median time to complete resolution in the per-attack analysis were 0.25 hours and 8.4 hours, respectively (Table 10), which were the shortest times among the various HAE attack locations.

Table 10. Time to Initial Onset of Symptom Relief and Time to Complete Resolution of HAE Symptoms for Laryngeal HAE Attacks
Statistic | Laryngeal (n=48)
Time to initial onset of symptom relief [hours]
Median (range) | 0.25 (0.10 - 1.25)
95% CI for median | [0.23; 0.42]
Time to complete resolution of HAE symptoms [hours]
Median (range) | 8.4 (0.6 - 61.8 [The maximum time to complete resolution of 61.8 hours was an imputed value. Subject 29301 had 2 laryngeal HAE attacks with missing times to complete resolution of HAE symptoms, which were imputed with the maximum time to complete resolution of HAE symptoms observed for an abdominal HAE attack in this subject.])
95% CI for median | [6.2; 21.5]
CI = confidence interval
HAE = hereditary angioedema
N = number of attacks

There were no clinically relevant or consistent data suggesting that gender, age group, race/ethnic group, type of HAE, routine use of androgens, or presence of detectable anti-C1 Esterase Inhibitor antibodies had an effect on the time to initial or complete relief of symptoms following BERINERT.

The prospective open-label extension study demonstrated that, in comparison to untreated historical control data retrospectively collected at a study center in Germany over a 20 year period^8, the BERINERT 20 IU/kg body weight dose appeared to be effective in ameliorating laryngeal HAE attacks by achieving complete resolution of HAE symptoms within 24 hours from attack onset in the majority of subjects. The treatment effects observed with BERINERT in the extension study are consistent with the findings from the placebo-controlled efficacy trial.

15 REFERENCES

1. German Medical Profession's Drugs Committee. Severe thrombus formation of BERINERT® HS. Deutsches Ärzteblatt. 2000;97:B-864.
2. Horstick, G et al. Application of C1-Esterase Inhibitor During Reperfusion of Ischemic Myocardium: Dose-Related Beneficial Versus Detrimental Effects. Circulation. 2001;104:3125-3131.
3. Martinez-Saguer I, Rusicke E, Aygören-Pürsün E, et al. Characterization of acute hereditary angioedema attacks during pregnancy and breast-feeding and their treatment with C1 inhibitor concentrate. Am J Obstet Gynecol. 2010;203:131.e1-7.
4. Carrell RW, Boswell DR. Serpins: the superfamily of plasma serine proteinase inhibitors. In: Barrett A, Salvesen G, eds. Proteinase Inhibitors. Amsterdam: Elsevier. 1986;12:403-420.
5. Harrison RA. Human C1 inhibitor: Improved isolation and preliminary structural characterization. Biochemistry 1983;22:5001-5007.
6. Davis AE, The pathophysiology of hereditary angioedema. Clin Immunol. 2005;114:3-9.
7. Nuijens JH, Eerenberg-Belmer AJM, Huijbregts CCM, et al. Proteolytic inactivation of plasma C1 inhibitor in sepsis. J Clin Invest. 1989;84:443-450.
8. Bork K, Barnstedt SE. Treatment of 193 Episodes of Laryngeal Edema with C1 Inhibitor Concentrate in Patients with Hereditary Angioedema. Arch Intern Med. 2001;161:714-718.

16 HOW SUPPLIED/STORAGE AND HANDLING

- BERINERT is supplied in a single-dose vial together with an administration kit.
- 500 IU vial of BERINERT for reconstitution with 10 mL of Sterile Water for Injection, USP.
- The components used in the packaging for BERINERT are not made with natural rubber latex.

Each product presentation includes a package insert and the following components:

Table 11. How Supplied
 | Carton NDC Number | Components
500 IU | 63833-825-02 | - BERINERT in a single-dose vial [NDC 63833-835-01] - 10 mL vial of Sterile Water for Injection, USP [NDC 63833-765-15] - 10 mL silicone-free syringe - IV set and butterfly needle - Mix2Vial filter transfer set - Alcohol swabs

Storage and Handling

- When stored at temperatures of 2-30°C (36-86°F), BERINERT is stable for the period indicated by the expiration date on the carton and vial label.
- Keep BERINERT in its original carton until ready to use.
- Do not freeze.
- Protect from light.
- Discard any unused product and all used disposable supplies.

17 PATIENT COUNSELING INFORMATION

Advise the patients to read the FDA-approved patient labeling (Patient Information).

Inform patients to immediately report the following to their physician:

- Signs and symptoms of allergic hypersensitivity reactions, such as hives, urticaria, tightness of the chest, wheezing, hypotension and/or anaphylaxis experienced during or after injection of BERINERT [see Warnings and Precautions (5.1)]
- Signs and symptoms of a thromboembolic event including pain and/or swelling of an arm or leg with warmth over the affected area, discoloration of an arm or leg, unexplained shortness of breath, chest pain or discomfort that worsens on deep breathing, unexplained rapid pulse, numbness or weakness on one side of the body. Advise patients with known risk factors for thromboembolic events that they are at an increased risk for these events [see Warnings and Precautions (5.2)].

- Advise female patients to notify their physician if they become pregnant or intend to become pregnant during the treatment of acute abdominal or facial HAE attacks with BERINERT [see Use in Specific Populations (8.1)].
- Advise patients to notify their physician if they are breastfeeding or plan to breastfeed [see Use in Specific Populations (8.2)].
- Advise patients to consult with their healthcare professional prior to travel.
- Advise patients/caregivers to bring an adequate supply of BERINERT when traveling.
- Advise patients to bring BERINERT with them when they visit a healthcare provider/facility for an acute HAE attack.
- Advise patients that, because BERINERT is made from human blood, it may carry a risk of transmitting infectious agents, e.g., viruses, the variant Creutzfeldt-Jakob disease (vCJD) agent and, theoretically, the Creutzfeldt-Jakob (CJD) agent [see Warnings and Precautions (5.3) and Description (11)]. Inform patients of the risks and benefits of BERINERT before prescribing or administering it to the patient.

Self-administration — Ensure that the patient (or caregiver) is an appropriate candidate for self-administration, this includes, but not limited to a determination that:

- The patient (or caregiver) is reliably able to recognize the signs and symptoms of their HAE attacks.
- The patient (or caregiver) has the necessary dexterity and comprehension to be trained to self-administer.

If self-administration is deemed appropriate, ensure that the patient/caregiver receives clear instructions and training on intravenous administration in the home or other appropriate setting and has demonstrated the ability to perform intravenous infusions.

- Ensure the patients/caregivers understand the importance of not starting self-administration if the HAE attack (regardless of type) has progressed to a point that the patient/caregiver would be unable to successfully prepare or administer BERINERT.
- Given the potential for airway obstruction during acute laryngeal HAE attacks, patients self-administering BERINERT should be advised to immediately seek medical attention in an appropriate healthcare facility in addition to treatment with BERINERT.
- To help exclude the possibility that another potentially serious medical cause may be responsible for their symptoms, advise patients self-administering BERINERT to contact their healthcare provider after treating suspected abdominal HAE attacks.
- Instruct patients/caregivers to record the lot number from the BERINERT vial label every time they use BERINERT.

The attached BERINERT "Patient Product Information (PPI)" contains more detailed instructions for patients/caregivers who will be self-administering BERINERT.

FDA-Approved Patient Labeling – Patient Product Information (PPI)

BERINERT (BEAR-ĭ-nert)
C1 Esterase Inhibitor (Human)
Freeze-Dried Powder for Reconstitution

This leaflet summarizes important information about BERINERT. Please read it carefully before using BERINERT and each time you get a refill. There may be new information provided. This information does not take the place of talking with your healthcare provider, and it does not include all of the important information about BERINERT. If you have any questions after reading this, ask your healthcare provider.

Do not attempt to self-administer unless you have been taught how by your healthcare provider.

What is BERINERT?

BERINERT is an injectable medicine used to treat swelling and/or painful HAE attacks in adults and children with Hereditary Angioedema (HAE). HAE is caused by the poor functioning or lack of a protein called C1 that is present in your blood and helps control inflammation (swelling) and parts of the immune system. BERINERT contains C1 esterase inhibitor, a protein that helps control C1.

Who should not use BERINERT?

You should not use BERINERT if you have experienced life-threatening immediate hypersensitivity reactions, including anaphylaxis, to the product.

What should I tell my healthcare provider before using BERINERT?

Tell your healthcare provider about all of your medical conditions, including if you:

- Are pregnant or planning to become pregnant. It is not known if BERINERT can harm your unborn baby.
- Are breastfeeding or plan to breastfeed. It is not known if BERINERT passes into your milk and if it can harm your baby.
- Have a history of blood clotting problems. Blood clots have occurred in patients receiving BERINERT. Very high doses of C1 esterase inhibitor could increase the risk of blood clots. Tell your healthcare provider if you have a history of heart or blood vessel disease, stroke, blood clots, or have thick blood, an indwelling catheter/access device in one of your veins, or have been immobile for some time. These things may increase your risk of having a blood clot after using BERINERT. Also, tell your healthcare provider what drugs you are using, as some drugs, such as birth control pills or certain androgens, may increase your risk of developing a blood clot.

Tell your healthcare provider and pharmacist about all of the medicines you take, including all prescription and non-prescription medicines such as over-the-counter medicines, supplements, or herbal remedies.

What are the possible side effects of BERINERT?

Allergic reactions may occur with BERINERT. Call your healthcare provider or seek emergency support services right away if you have any of the following symptoms after using BERINERT:

- wheezing
- difficulty breathing
- chest tightness
- turning blue (look at lips and gums)
- fast heartbeat
- swelling of the face
- faintness
- rash
- hives

Signs of a blood clot include:

- pain and/or swelling of an arm or leg with warmth over the affected area
- discoloration of an arm or leg
- unexplained shortness of breath
- chest pain or discomfort that worsens on deep breathing
- unexplained rapid pulse
- numbness or weakness on one side of the body.

In clinical studies, the most serious adverse reaction reported in subjects who received BERINERT was an increase in the severity of pain associated with HAE.

In clinical studies, the most common adverse reaction reported among subjects who received BERINERT in the placebo-controlled clinical trial was dysgeusia (bad taste in mouth).

Because BERINERT is made from human blood, it may carry a risk of transmitting infectious agents, such as viruses, the variant Creutzfeldt-Jakob disease (vCJD) agent and, theoretically, the Creutzfeldt-Jakob (CJD) agent.

These are not all the possible side effects of BERINERT.

Tell your healthcare provider about any side effect that bothers you or that does not go away. You can also report side effects to the FDA at 1-800-FDA-1088.

How should I store BERINERT?

- Keep BERINERT in its original carton to protect from light until ready to use.
- When stored at temperatures of 2-30°C (36-86°F), BERINERT is stable for the period indicated by the expiration date on the carton and vial label.
- Do not freeze.

What else should I know about BERINERT?

Medicines are sometimes prescribed for purposes other than those listed here. Do not use BERINERT for a condition for which it is not prescribed. Do not share BERINERT with other people, even if they have the same symptoms that you have.

This leaflet summarizes the most important information about BERINERT. If you would like more information, talk to your healthcare provider. You can ask your healthcare provider or pharmacist for information about BERINERT that was written for healthcare professionals. For more information, go to www.BERINERT.com or call 1-877-236-4423.

What are the symptoms of a facial, abdominal or laryngeal Hereditary Angioedema (HAE) attack?

Early HAE symptoms appear anywhere from minutes to one to two days before the attack worsens. HAE attacks can last hours to several days, and range in severity. Itching is not a typical feature of HAE attacks.

Facial attacks — These HAE attacks can occur in areas around the eyes and mouth, and result from local edema of tissue beneath the skin (subcutaneous).

Abdominal attacks — These HAE attacks appear as pain (colic), nausea, vomiting, and/or diarrhea. These symptoms result from the swelling of walls of the gastrointestinal tract.

Laryngeal HAE attacks — Laryngeal edema (swelling of the voice box, difficulty breathing, loss of voice, and noisy breathing on inspiration), can occur by itself, or with swelling of the lips, tongue, uvula (the piece of mouth tissue that hangs down from the top of the mouth over the back of the tongue), and soft palate (the soft tissue at the back of the mouth). Removing a tooth and oral surgery can trigger a laryngeal attack. Laryngeal swelling can develop in minutes or hours.

Many HAE attacks involve only one location of the body at a time, although combination attacks, such as cutaneous attacks that spread to involve the larynx (the voice box), can occur.

What other diseases or symptoms could resemble a HAE attack?

Some abdominal-related causes that can appear as an HAE attack include:

- Appendicitis
- Heartburn
- Gall bladder attack
- Diverticulitis
- Pancreatitis
- Stomach ulcer
- General abdominal distress

Other symptoms that can appear as an HAE attack include:

- Allergic reactions (e.g., insect bites and rash)

What should I know about self-administration?

- At the first symptoms of an attack, you should immediately prepare the prescribed dose of BERINERT for self-administration.
- You should not start self-administration if the HAE attack (regardless of type) has progressed to a point where you are unable to successfully dissolve BERINERT or to administer BERINERT.

Instructions for Use

- Do not attempt to self-administer unless you have been taught how by your healthcare provider.
- See the step-by-step instructions for injecting BERINERT at the end of this leaflet. You should always follow the specific instructions given by your healthcare provider. The steps listed below are general guidelines for using BERINERT. If you are unsure of the steps, please contact your healthcare provider or pharmacist before using.
- Your healthcare provider will prescribe the dose that you should administer, which is based on your body weight.
- After self-administering BERINERT for an acute laryngeal HAE attack, immediately seek medical attention in an appropriate healthcare facility after treatment with BERINERT.
- Contact your healthcare provider after treating suspected abdominal HAE attacks to help exclude the possibility that another potentially serious medical cause may be responsible for your symptoms.
- Call your healthcare provider right away if swelling is not controlled after using BERINERT.
- Bring BERINERT with you when you visit a healthcare provider/facility for an acute HAE attack.
- Talk to your healthcare provider before traveling to make sure you have an adequate supply of BERINERT.

Reconstitution and Administration

- Each BERINERT vial contains 500 IU of C1 esterase inhibitor as a lyophilized concentrate for reconstitution with 10 mL of Sterile Water for Injection, USP provided.
- Check the expiration date on the product vial label and on the administration kit. Do not use any component that is beyond the expiration date. Do not use if any components are damaged or opened.
- Use either the Mix2Vial transfer set provided with BERINERT or a commercially available double-ended needle and vented filter spike.
- Prepare and administer using aseptic techniques.
- After reconstitution and prior to administration inspect BERINERT. The reconstituted solution should be colorless, clear, and free from visible particles. Do not use if the solution is cloudy, discolored, or contains particulates.
- Use the silicone-free syringe provided.

Reconstitution

The procedures below are provided as general guidelines for the reconstitution of BERINERT.

1. Ensure that the BERINERT vial and diluent vial are at room temperature.
2. Place the BERINERT vial, diluent vial and Mix2Vial transfer set on a flat surface.
3. Remove the flip caps from the BERINERT and diluent vials. Wipe the vial stoppers with the alcohol swab provided. Allow to dry prior to opening the Mix2Vial transfer set package.
4. Open the Mix2Vial transfer set package by peeling away the lid (Figure 1). Leave the Mix2Vial transfer set in the clear package.
  Figure 1
5. Place the diluent vial on a flat surface and hold the vial tightly. Grip the Mix2Vial transfer set together with the clear package and push the plastic spike at the blue end of the Mix2Vial transfer set firmly through the center of the stopper of the diluent vial (Figure 2).
  Figure 2
6. Carefully remove the clear package from the Mix2Vial transfer set. Make sure that you pull up only the clear package, and not the Mix2Vial transfer set (Figure 3).
  Figure 3
7. With the BERINERT vial placed firmly on a flat surface, invert the diluent vial with the Mix2Vial transfer set attached and push the plastic spike of the transparent adapter firmly through the center of the stopper of the BERINERT vial (Figure 4). The diluent will automatically transfer into the BERINERT vial.
  Figure 4
8. With the diluent and BERINERT vial still attached to the Mix2Vial transfer set, gently swirl the BERINERT vial to ensure that the BERINERT is fully dissolved (Figure 5). Do not shake the vial.
  Figure 5
9. With one hand, grasp the BERINERT-side of the Mix2Vial transfer set and with the other hand grasp the blue diluent-side of the Mix2Vial transfer set and unscrew (counter clockwise) the set into two pieces (Figure 6).
  Figure 6
10. Carefully look at reconstituted solution in each vial of BERINERT. It should be colorless, clear, and free from visible particles. Do not use the vial if the liquid looks cloudy, contains particles, or has changed color. Do not use if the expiration date on the label has expired.
11. Draw air into the empty, sterile, silicone-free syringe provided. While the BERINERT vial is upright, screw the syringe to the Mix2Vial transfer set. Inject air into the BERINERT vial. While keeping the syringe plunger pressed, invert the system upside down and draw the concentrate into the syringe by pulling the plunger back slowly (Figure 7). If BERINERT is not immediately used, please store reconstituted solution in the vial.
  Figure 7
12. Now that the concentrate has been transferred into the syringe, firmly grasp the barrel of the syringe (keeping the plunger facing down) and unscrew (counter clockwise) the syringe from the Mix2Vial transfer set (Figure 8). Attach the syringe to a suitable intravenous administration set.
  Figure 8
13. If patient is to receive more than one vial, a new unused Mix2Vial transfer set and a new silicone-free syringe should be used for each BERINERT vial.
14. Do not refrigerate after reconstitution. When reconstitution is carried out using aseptic technique, administration may begin within 8 hours, provided the solution has been stored at up to 30°C (86°F). Do not refrigerate or freeze the reconstituted solution. Only store the reconstituted solution in the vial.

SELF-ADMINISTRATION (Intravenous Infusion)

Your healthcare provider will teach you how to safely administer BERINERT. It is important that BERINERT is injected directly into a visible vein. Do not inject into surrounding tissues or into an artery. Once you learn how to self-administer, follow the instructions provided below.

Step 1: Assemble supplies

Gather the following BERINERT supplies:

Provided with Administration Kit:

- silicone-free syringe
- IV set and butterfly needle
- alcohol swabs

Not provided:

- Tourniquet
- Sterile gauze and tape, or transparent dressing
- Bandage (adhesive dressing)
- Gloves (if recommended by your healthcare provider)
- Other items (sharps or other container, treatment diary or log book)

Step 2: Wash hands

- Thoroughly wash and dry your hands.
- If you have been told to wear gloves when preparing your infusion, put the gloves on.

Step 3: Clean surface

Thoroughly clean a table or other flat surface using one or more of the alcohol wipes.

Step 4: Prime the infusion set

As instructed by your healthcare provider:

- To prime (fill) the infusion tubing, connect the syringe filled with BERINERT to the infusion set tubing and gently push on the syringe plunger to fill the tubing with BERINERT (Figure 9).
  Figure 9

Step 5: Prepare the infusion site

- Apply a tourniquet above the site of the infusion.
- Prepare the infusion site by wiping the skin well with an alcohol swab and allow it to dry (Figure 10).
  Figure 10

Step 6: Infusion

As instructed by your healthcare provider:

- Insert the butterfly needle of the infusion set tubing into your vein (Figure 11).
  Figure 11
- If necessary, use sterile gauze and tape or transparent dressing to hold the needle in place.
- To make sure that the needle is in a vein, gently pull back on the syringe plunger and check to see if blood is in the tubing (Figure 12). If there is blood present, then the needle is in a vein. If there is no blood present, remove the needle and repeat this step using a new needle, new administration tubing, and a different injection site.
  Figure 12

- Remove the tourniquet.
- Inject the BERINERT solution slowly at a rate of approximately 4 mL per minute (Figure 13).
  Figure 13

After infusing the entire amount of BERINERT, remove the infusion set, per manufacturer instructions, (Figure 14) and cover the infusion site with a bandage (Figure 15), holding pressure on the site for a few minutes.

Figure 14
Figure 15

Step 7: Record treatment

- Record the lot number from the BERINERT vial label in your treatment diary or log book with the date and time of infusion every time you use BERINERT.

Step 8: Clean up

- Dispose of all unused solution, empty vials, used needles and syringe in an appropriate container. The container must be suitable for disposal of sharp waste that might hurt others if not handled correctly.

This Patient Package Insert has been approved by the US Food and Drug Administration.

Manufactured by:
CSL Behring GmbH
35041 Marburg, Germany
US License No. 1765

Distributed by:
CSL Behring LLC
Kankakee, IL 60901 USA

Mix2Vial® is a registered trademark of West Pharma. Services IL, Ltd., a subsidiary of West Pharmaceuticals Services, Inc.

PRINCIPAL DISPLAY PANEL - 500 IU Vial Label

NDC 63833-835-01

C1 Esterase
Inhibitor (Human)

BERINERT®

For Intravenous Use Only.

Manufactured by:
CSL Behring GmbH
35041 Marburg, Germany
US License No. 1765
Distributed by:
CSL Behring LLC
Kankakee, IL 60901 USA

Code

PRINCIPAL DISPLAY PANEL - Kit Carton

NDC 63833-825-02
One single-dose Vial and Sterile Water for Injection, USP
500 IU

C1 Esterase Inhibitor
(Human)

BERINERT®

For Intravenous Use Only.

Manufactured by:
CSL Behring GmbH
35041 Marburg, Germany
US License No. 1765
Distributed by:
CSL Behring LLC
Kankakee, IL 60901 USA

CSL Behring